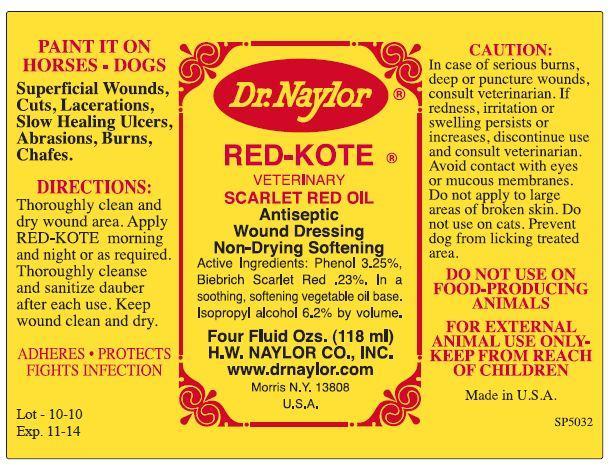 DRUG LABEL: RED-KOTE Veterinary Scarlet Red Oil 
NDC: 15878-213 | Form: LIQUID
Manufacturer: H. W. Naylor Company Inc.
Category: animal | Type: OTC ANIMAL DRUG LABEL
Date: 20150609

ACTIVE INGREDIENTS: Phenol 37.9 mg/1000 mL; Scarlet Red 2.4 mg/1000 mL
INACTIVE INGREDIENTS: Linseed Oil; Castor Oil; Isopropyl Alcohol

RED-KOTE® WOUND DRESSING

Active Ingredients

Phenol 3.25%, Biebrich Scarlet Red .23%

Purpose

Superficial Wounds, Cuts, Lacerations, Slow Healing Ulcers, Abrasions, Burns, Chafes.

Directions

PAINT IT ON HORSES • DOGS

Thoroughly clean and dry wound area. Apply RED-KOTE morning and night or as required.

Thoroughly cleanse and sanitize dauber after each use.

Keep wound clean and dry.

Safety

CAUTION: In case of serious burns, deep or puncture wounds, consult veterinarian.

If redness, irritation or swelling persists or increases, discontinue use and consult veterinarian.

Avoid contact with eyes or mucous membranes.

Do not apply to large areas of broken skin.

Do not use on cats.

Prevent dog from licking treated area.

DO NOT USE ON FOOD-PRODUCING ANIMALS.

FOR EXTERNAL ANIMAL USE ONLY.

Other Ingredients

Vegetable Oil Base, Isopropyl Alcohol

Questions?

www.drnaylor.com

Principal Display Panels

Dr. Naylor®
RED-KOTE® VETERINARY SCARLET RED OIL
Antiseptic Wound Dressing
Non-Drying Softening
Four Fluid Ozs. (118 grams)
H.W. NAYLOR CO., INC.
www.drnaylor.com
Morris N.Y. 13808
U.S.A.
Made in U.S.A.
SP5032
ADHERES • PROTECTS
FIGHTS INFECTION
Lot - 10-10
Exp. 11-14